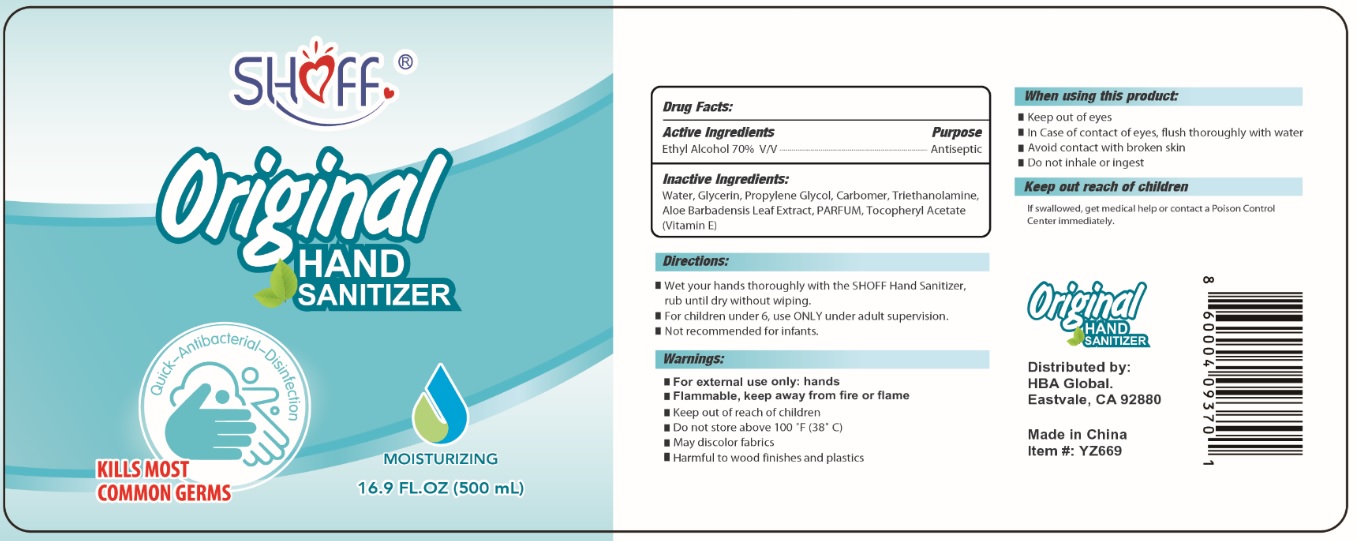 DRUG LABEL: SHOFF HAND SANITIZER
NDC: 78021-370 | Form: GEL
Manufacturer: HIMMELGEISTER INC. dba HBA Global
Category: otc | Type: HUMAN OTC DRUG LABEL
Date: 20200529

ACTIVE INGREDIENTS: ALCOHOL 70 mL/100 mL
INACTIVE INGREDIENTS: WATER; GLYCERIN; PROPYLENE GLYCOL; CARBOMER HOMOPOLYMER, UNSPECIFIED TYPE; TROLAMINE; ALOE VERA LEAF; .ALPHA.-TOCOPHEROL ACETATE

SHOff Original HAND SANITIZER

Active Ingredients

Ethyl Alcohol 70% V/V

Purpose

Antiseptic

Uses

- hand sanitizer to decrease bacteria on the skin

Inactive Ingredients:

Water, Glycerin, Propylene Glycol, Carbomer, Triethanolamine, Aloe Barbadensis Leaf Extract, PARFUM, Tocopheryl Acetate(Vitamin E)

Directions:

- Wet your hands thoroughly with the SHOFF Hand Sanitizer, rub until dry without wiping.
- For children under6, use ONLY under adult supervision.
- Not recommended for infants.

Warnings:

- For external use only: hands
- Flammable, keep away from fire or flame
- Keep out of reach of children
- Do not store above 100F(38C)
- May discolor fabrics
- Harmful to wood finishes and plastics

When using this product:

- Keep out of eyes
- In Case of contact of eyes, flush thoroughly with water
- Avoid contact with broken skin
- Do not inhale or ingest

Keep out of reach of children

If swallowed, get medical help or contact a Poison Control Center immediately.

Distributed by:

HBA Global.

Eastvale, CA 92880

Made in China

Item#: YZ669

860004093701

Quick-Antibacterial-Disinfection

KILLS MOST COMMON GERMS

MOISTURIZING